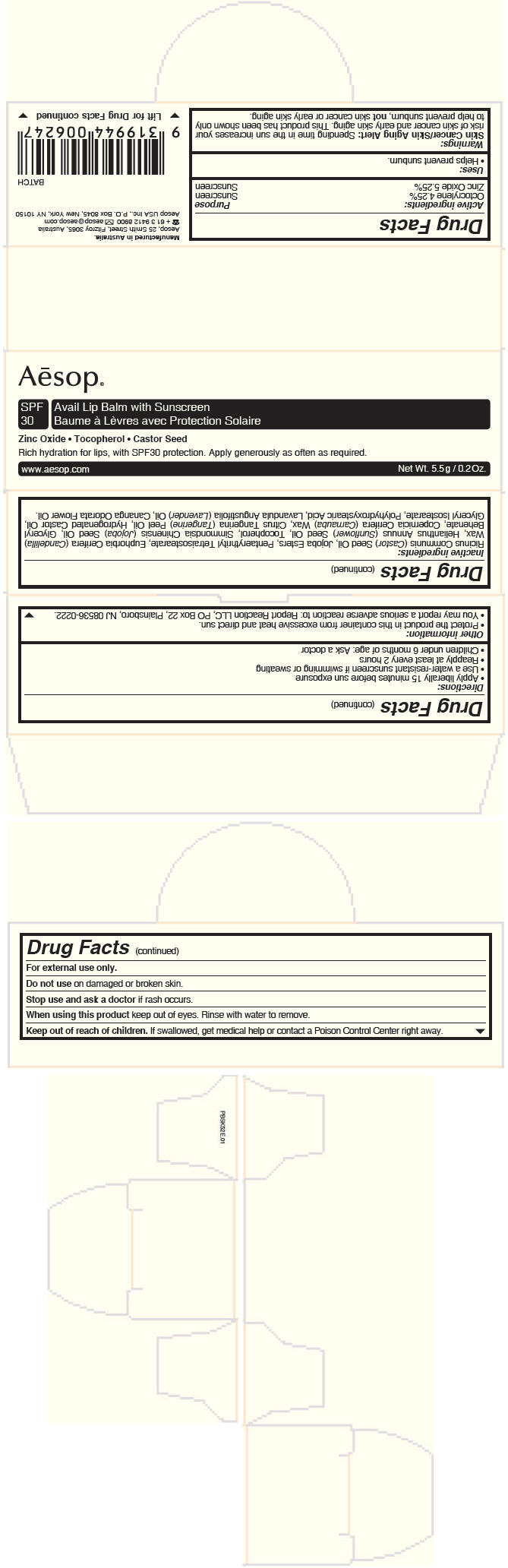 DRUG LABEL: Avail Lip Balm with Sunscreen
NDC: 76293-052 | Form: STICK
Manufacturer: Emeis Cosmetics Pty Ltd
Category: otc | Type: HUMAN OTC DRUG LABEL
Date: 20131031

ACTIVE INGREDIENTS: Zinc Oxide 0.00058 g/0.011 g; Octocrylene 0.00047 g/0.011 g
INACTIVE INGREDIENTS: Castor Oil; Hydrogenated Jojoba Oil/Jojoba Oil, Randomized (Iodine Value 57-61); Pentaerythrityl tetraisostearate; Candelilla Wax; Sunflower Oil; Tocopherol; Jojoba Oil; Glyceryl Dibehenate; Carnauba Wax; Mandarin Oil; Hydrogenated Castor Oil; Glyceryl Isostearate; Polyhydroxystearic Acid (2300 MW); Lavender Oil; Cananga Oil

Avail Lip Balm with Sunscreen

Drug Facts

ACTIVE INGREDIENT

Active ingredients: | Purpose
Octocrylene 4.25% | Sunscreen
Zinc Oxide 5.25% | Sunscreen

Uses

- Helps prevent sunburn.

Warnings

Skin Cancer/Skin Aging Alert

Spending time in the sun increases your risk of skin cancer and early skin aging. This product has been shown only to help prevent sunburn, not skin cancer or early skin aging.

For external use only.

Do not use on damaged or broken skin.

Stop use and ask a doctor if rash occurs.

When using this product keep out of eyes. Rinse with water to remove.

Keep out of reach of children. If swallowed, get medical help or contact a Poison Control Center right away.

Directions

- Apply liberally 15 minutes before sun exposure
- Use a water-resistant sunscreen if swimming or sweating
- Reapply at least every 2 hours
- Children under 6 months of age: Ask a doctor

Other information

- Protect the product in this container from excessive heat and direct sun.
- You may report a serious adverse reaction to: Report Reaction LLC, PO Box 22, Plainsboro, NJ 08536-0222.

Inactive ingredients

Ricinus Communis (Castor) Seed Oil, Jojoba Esters, Pentaerythrityl Tetraisostearate, Euphorbia Cerifera (Candelilla) Wax, Helianthus Annuus (Sunflower) Seed Oil, Tocopherol, Simmondsia Chinensis (Jojoba) Seed Oil, Glyceryl Behenate, Copernicia Cerifera (Carnauba) Wax, Citrus Tangerina (Tangerine) Peel Oil, Hydrogenated Castor Oil, Glyceryl Isostearate, Polyhydroxystearic Acid, Lavandula Angustifolia (Lavender) Oil, Cananga Odorata Flower Oil.

PRINCIPAL DISPLAY PANEL - 5.5 g Cylinder Carton

Aēsop®

SPF
30

Avail Lip Balm with Sunscreen

Zinc Oxide • Tocopherol • Castor Seed

Rich hydration for lips, with SPF30 protection. Apply generously as often as required.

www.aesop.com
Net Wt. 5.5 g / 0.2 Oz.